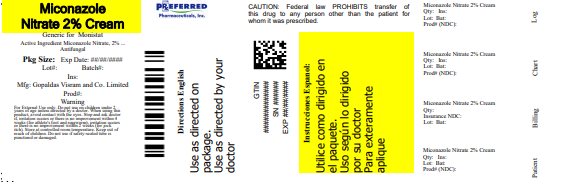 DRUG LABEL: Antifungal Cream
NDC: 68788-8645 | Form: CREAM
Manufacturer: Preferred Pharmaceuticals Inc.
Category: otc | Type: HUMAN OTC DRUG LABEL
Date: 20250811

ACTIVE INGREDIENTS: MICONAZOLE NITRATE 2 g/100 g
INACTIVE INGREDIENTS: EDETATE DISODIUM; CETOSTEARYL ALCOHOL; LIGHT MINERAL OIL; CHLOROCRESOL; PROPYLENE GLYCOL; WATER; WHITE PETROLATUM; SODIUM PHOSPHATE, DIBASIC, DIHYDRATE; SODIUM PHOSPHATE, MONOBASIC, DIHYDRATE; POLYOXYL 20 CETOSTEARYL ETHER

2% Miconazole Nitrate Cream, USP

Active ingredient

Miconazole Nitrate 2%

Purpose

Antifungal

Uses

- For the treatment of most athlete's foot (tinea pedis), jock itch (tinea cruris), Ringworm (tinea corporis).
- For the treatment of superficial skin infections caused by yeast (Candida Albicans)
- Relieves itching, scaling, burning, discomfort and chafing associated with jock itch or itching, burning feet.

Warnings

For external use only

Do not use

- On children under 2 years of age unless directed by a doctor

When using this product

- Avoid contact with the eyes

Stop use and ask a doctor if

- irritation occurs
- there is no improvement within 2 weeks when used for the treatment of jock itch
- there is no improvement within 4 weeks when used for athlete's foot and ringworm

Keep out of reach of children

If swallowed, get medical help or contact a Poison Control Centre right away.

Directions

- Clean the affected area and dry thoroughly.
- Apply a thin layer of the product over affected area twice daily (morning and night) or as directed by a doctor.
- Supervise children in the use of this product.
- For athlete's foot: pay special attention to spaces between the toes; wear well-fitting, ventilated shoes, and change shoes and socks at least once daily.
- For athlete's foot and ringworm, use daily for 4 weeks.
- For jock itch, use daily for 2 weeks.
- If condition persists longer, consult a doctor.
- This product is not effective on scalp or nails.

Other information

- Do not use if seal on the tube is damaged or is not visible. To open, unscrew cap, pull tab to remove foil seal.
- Store at controlled room temperature.
- Preserve in tight container.
- See crimp of tube or carton for Lot Number and expiry date.

Inactive ingredients

Cetostearyl Alcohol, Chlorocresol, Edetate Disodium, Light Mineral Oil, Macrogol Cetostearyl Ether 20, Propylene Glycol, Purified Water, Sodium Phosphate Dibasic Dihydrate, Sodium Phosphate Monobasic Dihydrate, White Petrolatum.

Questions?

Contact 1-800-707-4621

Manufactured in India by:

Gopaldas Visram and Company Limited.

Plot No. A327, T.T.C. Indl. Area, M.I.D.C.

Mahape, Navi Mumbai - 400710 Mfg. Lic. No.: KD/739

For BluePoint Laboratories

Relabeled By: Preferred Pharmaceuticals Inc.

NDC 68788-8645-2